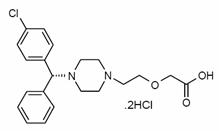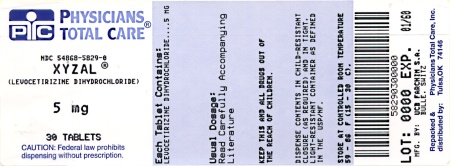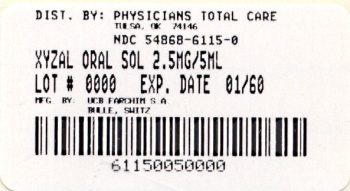 DRUG LABEL: Xyzal
NDC: 54868-5829 | Form: TABLET
Manufacturer: Physicians Total Care, Inc.
Category: prescription | Type: HUMAN PRESCRIPTION DRUG LABEL
Date: 20100511

ACTIVE INGREDIENTS: LEVOCETIRIZINE DIHYDROCHLORIDE 5 mg/1 1
INACTIVE INGREDIENTS: CELLULOSE, MICROCRYSTALLINE; LACTOSE MONOHYDRATE; MAGNESIUM STEARATE; HYPROMELLOSE; TITANIUM DIOXIDE

HIGHLIGHTS OF PRESCRIBING INFORMATION

These highlights do not include all the information needed to use XYZAL safely and effectively. See full prescribing information for XYZAL. XYZAL (levocetirizine dihydrochloride) 5 mg tablets 2.5 mg/5 mL (0.5 mg/mL) oral solution Initial U.S. Approval: 1995

RECENT MAJOR CHANGES

Indications and Usage, Seasonal Allergic Rhinitis (1.1) | 08/2009
Indications and Usage, Perennial Allergic Rhinitis (1.2) | 08/2009
Indications and Usage, Chronic Idiopathic Urticaria (1.3) | 08/2009
Dosage and Administration, Children 6 months to 5 Years (2.3) | 08/2009

1 INDICATIONS AND USAGE

XYZAL is a histamine H1‑receptor antagonist indicated for:

- The relief of symptoms associated with seasonal and perennial allergic rhinitis (1.1, 1.2)
- The treatment of the uncomplicated skin manifestations of chronic idiopathic urticaria (1.3)

2 DOSAGE AND ADMINISTRATION

- Adults and children 12 years of age and older: 5 mg once daily in the evening (2.1)
- Children 6 to 11 years of age: 2.5 mg once daily in the evening (2.2)
- Children 6 months to 5 years of age: 1.25 mg (1/2 teaspoon oral solution) [2.5mL] once daily in the evening (2.3)
- Renal Impairment Adjust the dose in patients 12 years of age and older with decreased renal function (2.4, 12.3)

3 DOSAGE FORMS AND STRENGTHS

- Immediate release breakable (scored) tablets, 5 mg (3)
- Immediate release oral solution, 2.5 mg per 5 mL (0.5 mg per mL) (3)

4 CONTRAINDICATIONS

- Patients with a known hypersensitivity to levocetirizine or any of the ingredients of XYZAL or to cetirizine (4)
- Patients with end-stage renal disease at less than 10 mL/min creatinine clearance or patients undergoing hemodialysis (4)
- Children 6 months to 11 years of age with renal impairment (4)

5 WARNINGS AND PRECAUTIONS

- Avoid engaging in hazardous occupations requiring complete mental alertness such as driving or operating machinery when taking XYZAL (5.1).
- Avoid concurrent use of alcohol or other central nervous system depressants with XYZAL (5.1).

6 ADVERSE REACTIONS

The most common adverse reactions (rate ≥2% and > placebo) were somnolence, nasopharyngitis, fatigue, dry mouth, and pharyngitis in subjects 12 years of age and older, and pyrexia, somnolence, cough, and epistaxis in children 6 to 12 years of age. In subjects 1 to 5 years of age, the most common adverse reactions (rate ≥2% and > placebo) were pyrexia, diarrhea, vomiting, and otitis media. In subjects 6 to 11 months of age, the most common adverse reactions (rate ≥3% and > placebo) were diarrhea and constipation. (6.1).

To report SUSPECTED ADVERSE REACTIONS, contact UCB, Inc. at 866-822-0068 or FDA at 1-800-FDA-1088 or www.fda.gov/medwatch.

7 DRUG INTERACTIONS

Enter highlights text here

8 USE IN SPECIFIC POPULATIONS

- Renal Impairment
  Because XYZAL is substantially excreted by the kidneys, the risk of adverse reactions to this drug may be greater in patients with impaired renal function (8.6 and 12.3).
- Pediatric Use
  Do not exceed the recommended doses of 2.5 mg and 1.25 mg once daily in children 6 to 11 years and 6 months to 5 years of age, respectively. Systemic exposure with these doses in respective pediatric age groups is comparable to that from a 5 mg once daily dose in adults. (12.3).

FULL PRESCRIBING INFORMATION

RECENT MAJOR CHANGES

Enter section text here

1 INDICATIONS AND USAGE

Enter section text here

1.1 Seasonal Allergic Rhinitis

XYZAL® is indicated for the relief of symptoms associated with seasonal allergic rhinitis in adults and children 2 years of age and older.

1.2 Perennial Allergic Rhinitis

XYZAL is indicated for the relief of symptoms associated with perennial allergic rhinitis in adults and children 6 months of age and older.

1.3 Chronic Idiopathic Urticaria

XYZAL is indicated for the treatment of the uncomplicated skin manifestations of chronic idiopathic urticaria in adults and children 6 months of age and older.

2 DOSAGE AND ADMINISTRATION

XYZAL is available as 2.5 mg/5 mL (0.5 mg/mL) oral solution and as 5 mg breakable (scored) tablets, allowing for the administration of 2.5 mg, if needed. XYZAL can be taken without regard to food consumption.

2.1 Adults and Children 12 Years of Age and Older

The recommended dose of XYZAL is 5 mg (1 tablet or 2 teaspoons [10 mL] oral solution) once daily in the evening. Some patients may be adequately controlled by 2.5 mg (1/2 tablet or 1 teaspoon [5 mL] oral solution) once daily in the evening.

2.2 Children 6 to 11 Years of Age

The recommended dose of XYZAL is 2.5 mg (1/2 tablet or 1 teaspoon [5 mL] oral solution) once daily in the evening. The 2.5 mg dose should not be exceeded because the systemic exposure with 5 mg is approximately twice that of adults [see Clinical Pharmacology (12.3)].

2.3 Children 6 months to 5 Years of A

The recommended initial dose of XYZAL is 1.25 mg (1/2 teaspoon oral solution) [2.5mL] once daily in the evening. The 1.25 mg once daily dose should not be exceeded based on comparable exposure to adults receiving 5 mg [see Clinical Pharmacology (12.3)].

2.4 Dose Adjustment for Renal and Hepatic Impairment

In adults and children 12 years of age and older with:

- Mild renal impairment (creatinine clearance [CLCR] = 50-80 mL/min): a dose of 2.5 mg once daily is recommended;
- Moderate renal impairment (CLCR = 30-50 mL/min): a dose of 2.5 mg once every other day is recommended;
- Severe renal impairment (CLCR = 10-30 mL/min): a dose of 2.5 mg twice weekly (administered once every 3-4 days) is recommended;
- End-stage renal disease patients (CLCR less than 10 mL/min) and patients undergoing hemodialysis should not receive XYZAL.

No dose adjustment is needed in patients with solely hepatic impairment. In patients with both hepatic impairment and renal impairment, adjustment of the dose is recommended.

3 DOSAGE FORMS AND STRENGTHS

XYZAL oral solution is a clear, colorless liquid containing 0.5 mg of levocetirizine dihydrochloride per mL.

XYZAL tablets are white, film‑coated, oval-shaped, scored, imprinted (with the letter Y in red color on both halves of the scored tablet) and contain 5 mg levocetirizine dihydrochloride.

4 CONTRAINDICATIONS

The use of XYZAL is contraindicated in:

4.1 Patients with known hypersensitivity

Patients with known hypersensitivity to levocetirizine or any of the ingredients of XYZAL, or to cetirizine. Observed reactions range from urticaria to anaphylaxis [see Adverse Reactions (6.2)].

4.2 Patients with end-stage renal disease

Patients with end-stage renal disease (CLCR less than 10 mL/min) and patients undergoing hemodialysis

4.3 Pediatric patients with impaired renal function

Children 6 months to 11 years of age with impaired renal function

5 WARNINGS AND PRECAUTIONS

Enter section text here

5.1 Activities Requiring Mental Alertness

In clinical trials the occurrence of somnolence, fatigue, and asthenia has been reported in some patients under therapy with XYZAL. Patients should be cautioned against engaging in hazardous occupations requiring complete mental alertness, and motor coordination such as operating machinery or driving a motor vehicle after ingestion of XYZAL. Concurrent use of XYZAL with alcohol or other central nervous system depressants should be avoided because additional reductions in alertness and additional impairment of central nervous system performance may occur.

6 ADVERSE REACTIONS

Use of XYZAL has been associated with somnolence, fatigue, and asthenia [seeWarnings and Precautions (5.1)].

6.1 Clinical Trials Experience

The safety data described below reflect exposure to XYZAL in 2708 patients with seasonal or perennial allergic rhinitis or chronic idiopathic urticaria in 14 controlled clinical trials of 1 week to 6 months duration.

The short-term (exposure up to 6 weeks) safety data for adults and adolescents are based upon eight clinical trials in which 1896 patients (825 males and 1071 females aged 12 years and older) were treated with XYZAL 2.5, 5, or 10 mg once daily in the evening.

The short-term safety data from pediatric patients are based upon two clinical trials in which 243 children with seasonal or perennial allergic rhinitis (162 males and 81 females 6 to 12 years of age) were treated with XYZAL 5 mg once daily for 4 to 6 weeks, one clinical trial in which 114 children (65 males and 49 females 1 to 5 years of age) with allergic rhinitis or chronic idiopathic urticaria were treated with XYZAL 1.25 mg twice daily for 2 weeks, and one clinical trial in which 45 children (28 males and 17 females 6 to 11 months of age) with symptoms of allergic rhinitis or chronic urticaria were treated with XYZAL 1.25 mg once daily for 2 weeks.

The long-term (exposure of 4 or 6 months) safety data in adults and adolescents are based upon two clinical trials in which 428 patients (190 males and 238 females) with allergic rhinitis were exposed to treatment with XYZAL 5 mg once daily. Long term safety data are also available from an 18-month trial in 255 XYZAL-treated subjects 12-24 months of age.

Because clinical trials are conducted under widely varying conditions, adverse reaction rates observed in the clinical trials of a drug cannot be directly compared to rates in the clinical trial of another drug and may not reflect the rates observed in practice.

Adults and Adolescents 12 years of Age and Older

In studies up to 6 weeks in duration, the mean age of the adult and adolescent patients was 32 years, 44% of the patients were men and 56% were women, and the large majority (more than 90%) was Caucasian.

In these trials 43% and 42% of the subjects in the XYZAL 2.5 mg and 5 mg groups, respectively, had at least one adverse event compared to 43% in the placebo group.

In placebo-controlled trials of 1-6 weeks in duration, the most common adverse reactions were somnolence, nasopharyngitis, fatigue, dry mouth, and pharyngitis, and most were mild to moderate in intensity. Somnolence with XYZAL showed dose ordering between tested doses of 2.5, 5 and 10 mg and was the most common adverse reaction leading to discontinuation (0.5%).

Table 1 lists adverse reactions that were reported in greater than or equal to 2% of subjects aged 12 years and older exposed to XYZAL 2.5 mg or 5 mg in eight placebo-controlled clinical trials and that were more common with XYZAL than placebo.

Table 1 Adverse Reactions Reported in ≥ 2%* of Subjects Aged 12 Years and Older Exposed to XYZAL 2.5 mg or 5 mg Once Daily in Placebo-Controlled Clinical Trials 1-6 Weeks in Duration
Adverse Reactions | XYZAL 2.5 mg (n = 421) | XYZAL 5 mg (n = 1070) | Placebo (n = 912)
Somnolence | 22 (5%) | 61 (6%) | 16 (2%)
Nasopharyngitis | 25 (6%) | 40 (4%) | 28 (3%)
Fatigue | 5 (1%) | 46 (4%) | 20 (2%)
Dry Mouth | 12 (3%) | 26 (2%) | 11 (1%)
Pharyngitis | 10 (2%) | 12 (1%) | 9 (1%)

* Rounded to the closest unit percentage

Additional adverse reactions of medical significance observed at a higher incidence than in placebo in adults and adolescents aged 12 years and older exposed to XYZAL are syncope (0.2%) and weight increased (0.5%).

Pediatric Patients 6 to 12 Years of Age

A total of 243 pediatric patients 6 to 12 years of age received XYZAL 5 mg once daily in two short-term placebo controlled double-blind trials. The mean age of the patients was 9.8 years, 79 (32%) were 6 to 8 years of age, and 50% were Caucasian. Table 2 lists adverse reactions that were reported in greater than or equal to 2% of subjects aged 6 to 12 years exposed to XYZAL 5 mg in placebo-controlled clinical trials and that were more common with XYZAL than placebo.

Table 2 Adverse Reactions Reported in ≥2%* of Subjects Aged 6-12 Years Exposed to XYZAL 5 mg Once Daily in Placebo-Controlled Clinical Trials 4 and 6 Weeks in Duration
Adverse Reactions | XYZAL 5 mg (n = 243) | Placebo (n = 240)
Pyrexia | 10 (4%) | 5 (2%)
Cough | 8 (3%) | 2 (less than 1%)
Somnolence | 7 (3%) | 1 (less than 1%)
Epistaxis | 6 (2%) | 1 (less than 1%)

* Rounded to the closest unit percentage

Pediatric Patients 1 to 5 Years of Age

A total of 114 pediatric patients 1 to 5 years of age received XYZAL 1.25 mg twice daily in a two week placebo-controlled double-blind safety trial. The mean age of the patients was 3.8 years, 32% were 1 to 2 years of age, 71% were Caucasian and 18% were Black. Table 3 lists adverse reactions that were reported in greater than or equal to 2% of subjects aged 1 to 5 years exposed to XYZAL 1.25 mg twice daily in the placebo-controlled safety trial and that were more common with XYZAL than placebo.

Table 3 Adverse Reactions Reported in ≥2%* of Subjects Aged 1-5 Years Exposed to XYZAL 1.25 mg Twice Daily in a 2-Week Placebo-Controlled Clinical Trial
Adverse Reactions | XYZAL 1.25 mg Twice Daily (n = 114) | Placebo (n = 59)
Pyrexia | 5 (4%) | 1 (2%)
Diarrhea | 4 (4%) | 2 (3%)
Vomiting | 4 (4%) | 2 (3%)
Otitis Media | 3 (3%) | 0 (0%)

* Rounded to the closest unit percentage

Pediatric Patients 6 to 11 Months of Age

A total of 45 pediatric patients 6 to 11 months of age received XYZAL 1.25 mg once daily in a two week placebo-controlled double-blind safety trial. The mean age of the patients was 9 months, 51% were Caucasian and 31% were Black. Adverse reactions that were reported in more than 1 subject (i.e. greater than or equal to 3% of subjects) aged 6 to 11 months exposed to XYZAL 1.25 mg once daily in the placebo-controlled safety trial and that were more common with XYZAL than placebo included diarrhea and constipation which were reported in 6 (13%) and 1 (4%) and 3 (7%) and 1 (4%) children in the XYZAL and placebo-treated groups, respectively.

Long-Term Clinical Trials Experience

In two controlled clinical trials, 428 patients (190 males and 238 females) aged 12 years and older were treated with XYZAL 5 mg once daily for 4 or 6 months. The patient characteristics and the safety profile were similar to that seen in the short-term studies. Ten (2.3%) patients treated with XYZAL discontinued because of somnolence, fatigue or asthenia compared to 2 (less than 1%) in the placebo group.

There are no long term clinical trials in children below 12 years of age with allergic rhinitis or chronic idiopathic urticaria.

Laboratory Test Abnormalities

Elevations of blood bilirubin and transaminases were reported in less than 1% of patients in the clinical trials. The elevations were transient and did not lead to discontinuation in any patient.

6.2 Post-Marketing Experience

In addition to the adverse reactions reported during clinical trials and listed above, adverse events have also been identified during post-approval use of XYZAL in other countries. Because these events are reported voluntarily from a population of uncertain size, it is not always possible to reliably estimate their frequency or establish a causal relationship to drug exposure. Adverse events of hypersensitivity and anaphylaxis, angioneurotic edema, fixed drug eruption, pruritus, rash, and urticaria, convulsion, aggression and agitation, visual disturbances, palpitations, dyspnea, nausea, hepatitis, and myalgia have been reported.

Besides these events reported under treatment with XYZAL, other potentially severe adverse events have been reported from the post-marketing experience with cetirizine. Since levocetirizine is the principal pharmacologically active component of cetirizine, one should take into account the fact that the following adverse events could also potentially occur under treatment with XYZAL: hallucinations, suicidal ideation, orofacial dyskinesia, severe hypotension, cholestasis, glomerulonephritis, and still birth.

7 DRUG INTERACTIONS

In vitro data indicate that levocetirizine is unlikely to produce pharmacokinetic interactions through inhibition or induction of liver drug-metabolizing enzymes. No in vivo drug-drug interaction studies have been performed with levocetirizine. Drug interaction studies have been performed with racemic cetirizine.

7.1 Antipyrine, Azithromycin, Cimetidine, Erythromycin, Ketoconazole, Theophylline, and Pseudoephedrine

Pharmacokinetic interaction studies performed with racemic cetirizine demonstrated that cetirizine did not interact with antipyrine, pseudoephedrine, erythromycin, azithromycin, ketoconazole, and cimetidine. There was a small decrease (~16%) in the clearance of cetirizine caused by a 400 mg dose of theophylline. It is possible that higher theophylline doses could have a greater effect.

7.2 Ritonavir

Ritonavir increased the plasma AUC of cetirizine by about 42% accompanied by an increase in half-life (53%) and a decrease in clearance (29%) of cetirizine. The disposition of ritonavir was not altered by concomitant cetirizine administration.

8 USE IN SPECIFIC POPULATIONS

Enter section text here

8.1 Pregnancy

Pregnancy Category B

There are no adequate and well-controlled studies in pregnant women. Because animal reproduction studies are not always predictive of human response, XYZAL should be used during pregnancy only if clearly needed.

Teratogenic Effects:

In rats and rabbits, levocetirizine was not teratogenic at oral doses approximately 320 and 390, respectively, times the maximum recommended daily oral dose in adults on a mg/m^2 basis.

8.3 Nursing Mothers

No peri- and post-natal animal studies have been conducted with levocetirizine. In mice, cetirizine caused retarded pup weight gain during lactation at an oral dose in dams that was approximately 40 times the maximum recommended daily oral dose in adults on a mg/m^2 basis. Studies in beagle dogs indicated that approximately 3% of the dose of cetirizine was excreted in milk. Cetirizine has been reported to be excreted in human breast milk. Because levocetirizine is also expected to be excreted in human milk, use of XYZAL in nursing mothers is not recommended.

8.4 Pediatric Use

The recommended dose of XYZAL for the treatment of the uncomplicated skin manifestations of chronic idiopathic urticaria in patients 6 months to 17 years of age is based on extrapolation of efficacy from adults 18 years of age and older [see Clinical Studies (14)].

The recommended dose of XYZAL in patients 6 months to 11 years of age for the treatment of the symptoms of perennial allergic rhinitis and chronic idiopathic urticaria and in patients 2 to 11 years of age for the treatment of the symptoms of seasonal allergic rhinitis is based on cross-study comparisons of the systemic exposure of XYZAL in adults and pediatric patients and on the safety profile of XYZAL in both adult and pediatric patients at doses equal to or higher than the recommended dose for patients 6 months to 11 years of age.

The safety of XYZAL 5 mg once daily was evaluated in 243 pediatric patients 6 to 12 years of age in two placebo-controlled clinical trials lasting 4 and 6 weeks. The safety of XYZAL 1.25 mg twice daily was evaluated in one 2-week clinical trial in 114 pediatric patients 1 to 5 years of age and the safety of XYZAL 1.25 mg once daily was evaluated in one 2-week clinical trial in 45 pediatric patients 6 to 11 months of age [see Adverse Reactions (6.1)].

The effectiveness of XYZAL 1.25 mg once daily (6 months to 5 years of age) and 2.5 mg once daily (6 to 11 years of age) for the treatment of the symptoms of seasonal and perennial allergic rhinitis and chronic idiopathic urticaria is supported by the extrapolation of demonstrated efficacy of XYZAL 5 mg once daily in patients 12 years of age and older and based on the pharmacokinetic comparison between adults and children.

Cross-study comparisons indicate that administration of a 5 mg dose of XYZAL to 6 to 12 year old pediatric seasonal allergic rhinitis patients resulted in about 2-fold the systemic exposure (AUC) observed when 5 mg of XYZAL was administered to healthy adults. Therefore, in children 6 to 11 years of age the recommended dose of 2.5 mg once daily should not be exceeded. In a population pharmacokinetics study the administration of 1.25 mg once daily in children 6 months to 5 years of age resulted in systemic exposure comparable to 5 mg once daily in adults. [see Dosage and Administration (2.2); Clinical Studies (14); and Clinical Pharmacology (12.3)].

8.5 Geriatric Use

Clinical studies of XYZAL for each approved indication did not include sufficient numbers of patients aged 65 years and older to determine whether they respond differently than younger patients. Other reported clinical experience has not identified differences in responses between the elderly and younger patients. In general, dose selection for an elderly patient should be cautious, usually starting at the low end of the dosing range reflecting the greater frequency of decreased hepatic, renal, or cardiac function and of concomitant disease or other drug therapy.

8.6 Renal Impairment

XYZAL is known to be substantially excreted by the kidneys and the risk of adverse reactions to this drug may be greater in patients with impaired renal function. Because elderly patients are more likely to have decreased renal function, care should be taken in dose selection and it may be useful to monitor renal function [see Dosage and Administration (2) and Clinical Pharmacology (12.3)].

8.7 Hepatic Impairment

As levocetirizine is mainly excreted unchanged by the kidneys, it is unlikely that the clearance of levocetirizine is significantly decreased in patients with solely hepatic impairment [see Clinical Pharmacology (12.3)].

10 OVERDOSAGE

Overdosage has been reported with XYZAL.

Symptoms of overdose may include drowsiness in adults and initially agitation and restlessness, followed by drowsiness in children. There is no known specific antidote to XYZAL. Should overdose occur, symptomatic or supportive treatment is recommended. XYZAL is not effectively removed by dialysis, and dialysis will be ineffective unless a dialyzable agent has been concomitantly ingested.

The acute maximal non-lethal oral dose of levocetirizine was 240 mg/kg in mice (approximately 190 times the maximum recommended daily oral dose in adults, approximately 230 times the maximum recommended daily oral dose in children 6 to 11 years of age, and approximately 180 times the maximum recommended daily oral dose in children 6 months to 5 years of age on a mg/m^2 basis). In rats the maximal non-lethal oral dose was 240 mg/kg (approximately 390 times the maximum recommended daily oral dose in adults, approximately 460 times the maximum recommended daily oral dose in children 6 to 11 years of age, and approximately 370 times the maximum recommended daily oral dose in children 6 months to 5 years of age on a mg/m^2 basis).

11 DESCRIPTION

Levocetirizine dihydrochloride, the active component of XYZAL tablets and oral solution, is an orally active H1‑receptor antagonist. The chemical name is (R)-[2-[4-[(4-chlorophenyl) phenylmethyl]-1-piperazinyl] ethoxy] acetic acid dihydrochloride. Levocetirizine dihydrochloride is the R enantiomer of cetirizine hydrochloride, a racemic compound with antihistaminic properties. The empirical formula of levocetirizine dihydrochloride is C21H25ClN2O3•2HCl. The molecular weight is 461.82 and the chemical structure is shown below:

Levocetirizine dihydrochloride is a white, crystalline powder and is water soluble.

XYZAL 5 mg tablets are formulated as immediate release, white, film-coated, oval-shaped scored tablets for oral administration. The tablets are imprinted on both halves of the scored line with the letter Y in red (Opacode® Red). Inactive ingredients are: microcrystalline cellulose, lactose monohydrate, colloidal anhydrous silica, and magnesium stearate. The film coating contains hypromellose, titanium dioxide, and macrogol 400.

XYZAL 0.5 mg/mL oral solution is formulated as an immediate release, clear, colorless liquid. Inactive ingredients are: sodium acetate trihydrate, glacial acetic acid, maltitol solution, glycerin, methylparaben, propylparaben, saccharin, flavoring (consisting of triacetin, natural & artificial flavors, dl-alpha-tocopherol), purified water.

12 CLINICAL PHARMACOLOGY

Enter section text here

12.1 Mechanism of Action

Levocetirizine, the active enantiomer of cetirizine, is an anti-histamine; its principal effects are mediated via selective inhibition of H1 receptors. The antihistaminic activity of levocetirizine has been documented in a variety of animal and human models. In vitro binding studies revealed that levocetirizine has an affinity for the human H1-receptor 2-fold higher than that of cetirizine (Ki = 3 nmol/L vs. 6 nmol/L, respectively). The clinical relevance of this finding is unknown.

12.2 Pharmacodynamics

Studies in adult healthy subjects showed that levocetirizine at doses of 2.5 mg and 5 mg inhibited the skin wheal and flare caused by the intradermal injection of histamine. In contrast, dextrocetirizine exhibited no clear change in the inhibition of the wheal and flare reaction. Levocetirizine at a dose of 5 mg inhibited the wheal and flare caused by intradermal injection of histamine in 14 pediatric subjects (aged 6 to 11 years) and the activity persisted for at least 24 hours. The clinical relevance of histamine wheal skin testing is unknown.

A QT/QTc study using a single dose of 30 mg of levocetirizine did not demonstrate an effect on the QTc interval. While a single dose of levocetirizine had no effect, the effects of levocetirizine may not be at steady state following single dose. The effect of levocetirizine on the QTc interval following multiple dose administration is unknown. Levocetirizine is not expected to have QT/QTc effects because of the results of QTc studies with cetirizine and the long post-marketing history of cetirizine without reports of QT prolongation.

12.3 Pharmacokinetics

Levocetirizine exhibited linear pharmacokinetics over the therapeutic dose range in adult healthy subjects.

• Absorption

Levocetirizine is rapidly and extensively absorbed following oral administration. In adults, peak plasma concentrations are achieved 0.9 hour after administration of the oral tablet. The accumulation ratio following daily oral administration is 1.12 with steady state achieved after 2 days. Peak concentrations are typically 270 ng/mL and 308 ng/mL following a single and a repeated 5 mg once daily dose, respectively. Food had no effect on the extent of exposure (AUC) of the levocetirizine tablet, but Tmax was delayed by about 1.25 hours and Cmax was decreased by about 36% after administration with a high fat meal; therefore, levocetirizine can be administered with or without food.

A dose of 5 mg (10 mL) of XYZAL oral solution is bioequivalent to a 5 mg dose of XYZAL tablets. Following oral administration of a 5 mg dose of XYZAL oral solution to healthy adult subjects, the mean peak plasma concentrations were achieved approximately 0.5 hour post-dose.

• Distribution

The mean plasma protein binding of levocetirizine in vitro ranged from 91 to 92%, independent of concentration in the range of 90-5000 ng/mL, which includes the therapeutic plasma levels observed. Following oral dosing, the average apparent volume of distribution is approximately 0.4 L/kg, representative of distribution in total body water.

• Metabolism

The extent of metabolism of levocetirizine in humans is less than 14% of the dose and therefore differences resulting from genetic polymorphism or concomitant intake of hepatic drug metabolizing enzyme inhibitors are expected to be negligible. Metabolic pathways include aromatic oxidation, N- and O-dealkylation, and taurine conjugation. Dealkylation pathways are primarily mediated by CYP 3A4 while aromatic oxidation involves multiple and/or unidentified CYP isoforms.

• Elimination

The plasma half-life in adult healthy subjects was about 8 to 9 hours after administration of oral tablets and oral solution, and the mean oral total body clearance for levocetirizine was approximately 0.63 mL/kg/min. The major route of excretion of levocetirizine and its metabolites is via urine, accounting for a mean of 85.4% of the dose. Excretion via feces accounts for only 12.9% of the dose. Levocetirizine is excreted both by glomerular filtration and active tubular secretion. Renal clearance of levocetirizine correlates with that of creatinine clearance. In patients with renal impairment the clearance of levocetirizine is reduced [see Dosage and Administration (2.3)].

• Drug Interaction Studies

In vitro data on metabolite interaction indicate that levocetirizine is unlikely to produce, or be subject to metabolic interactions. Levocetirizine at concentrations well above Cmax level achieved within the therapeutic dose ranges is not an inhibitor of CYP isoenzymes 1A2, 2C9, 2C19, 2A1, 2D6, 2E1, and 3A4, and is not an inducer of UGT1A or CYP isoenzymes 1A2, 2C9 and 3A4.

No formal in vivo drug interaction studies have been performed with levocetirizine. Studies have been performed with the racemic cetirizine [see Drug Interactions (7)].

• Pediatric Patients

Data from a pediatric pharmacokinetic study with oral administration of a single dose of 5 mg levocetirizine in 14 children age 6 to 11 years with body weight ranging between 20 and 40 kg show that Cmax and AUC values are about 2-fold greater than that reported in healthy adult subjects in a cross-study comparison. The mean Cmax was 450 ng/mL, occurring at a mean time of 1.2 hours, weight-normalized, total body clearance was 30% greater, and the elimination half-life 24% shorter in this pediatric population than in adults.

Dedicated pharmacokinetic studies have not been conducted in pediatric patients younger than 6 years of age. A retrospective population pharmacokinetic analysis was conducted in 324 subjects (181 children 1 to 5 years of age, 18 children 6 to 11 years of age, and 124 adults 18 to 55 years of age) who received single or multiple doses of levocetirizine ranging from 1.25 mg to 30 mg. Data generated from this analysis indicated that administration of 1.25 mg once daily to children 6 months to 5 years of age results in plasma concentrations similar to those of adults receiving 5 mg once daily.

• Geriatric Patients

Limited pharmacokinetic data are available in elderly subjects. Following once daily repeat oral administration of 30 mg levocetirizine for 6 days in 9 elderly subjects (65–74 years of age), the total body clearance was approximately 33% lower compared to that in younger adults. The disposition of racemic cetirizine has been shown to be dependent on renal function rather than on age. This finding would also be applicable for levocetirizine, as levocetirizine and cetirizine are both predominantly excreted in urine. Therefore, the XYZAL dose should be adjusted in accordance with renal function in elderly patients [see Dosage and Administration (2)].

• Gender

Pharmacokinetic results for 77 patients (40 men, 37 women) were evaluated for potential effect of gender. The half-life was slightly shorter in women (7.08 ± 1.72 hr) than in men (8.62 ± 1.84 hr); however, the body weight-adjusted oral clearance in women (0.67 ± 0.16 mL/min/kg) appears to be comparable to that in men (0.59 ± 0.12 mL/min/kg). The same daily doses and dosing intervals are applicable for men and women with normal renal function.

• Race

The effect of race on levocetirizine has not been studied. As levocetirizine is primarily renally excreted, and there are no important racial differences in creatinine clearance, pharmacokinetic characteristics of levocetirizine are not expected to be different across races. No race-related differences in the kinetics of racemic cetirizine have been observed.

• Renal Impairment

Levocetirizine exposure (AUC) exhibited 1.8-, 3.2-, 4.3-, and 5.7-fold increase in mild, moderate, severe, renal impaired, and end-stage renal disease patients, respectively, compared to healthy subjects. The corresponding increases of half-life estimates were 1.4-, 2.0-, 2.9-, and 4-fold, respectively.

The total body clearance of levocetirizine after oral dosing was correlated to the creatinine clearance and was progressively reduced based on severity of renal impairment. Therefore, it is recommended to adjust the dose and dosing intervals of levocetirizine based on creatinine clearance in patients with mild, moderate, or severe renal impairment. In end-stage renal disease patients (CLCR less than 10 mL/min) levocetirizine is contraindicated. The amount of levocetirizine removed during a standard 4‑hour hemodialysis procedure was less than 10%.

The dosage of XYZAL should be reduced in patients with mild renal impairment. Both the dosage and frequency of administration should be reduced in patients with moderate or severe renal impairment [see Dosage and Administration (2.4)].

• Hepatic Impairment

XYZAL has not been studied in patients with hepatic impairment. The non-renal clearance (indicative of hepatic contribution) was found to constitute about 28% of the total body clearance in healthy adult subjects after oral administration.

As levocetirizine is mainly excreted unchanged by the kidney, it is unlikely that the clearance of levocetirizine is significantly decreased in patients with solely hepatic impairment [see Dosage and Administration (2)].

13 NONCLINICAL TOXICOLOGY

Enter section text here

13.1 Carcinogenesis, Mutagenesis, Impairment of Fertility

No carcinogenicity studies have been performed with levocetirizine. However, evaluation of cetirizine carcinogenicity studies are relevant for determination of the carcinogenic potential of levocetirizine. In a 2-year carcinogenicity study, in rats, cetirizine was not carcinogenic at dietary doses up to 20 mg/kg (approximately 15 times the maximum recommended daily oral dose in adults, approximately 10 times the maximum recommended daily oral dose in children 6 to 11 years of age and approximately 15 times the maximum recommended daily oral dose in children 6 months to 5 years of age on a mg/m^2 basis). In a 2-year carcinogenicity study in mice, cetirizine caused an increased incidence of benign hepatic tumors in males at a dietary dose of 16 mg/kg (approximately 6 times the maximum recommended daily oral dose in adults, approximately 4 times the maximum recommended daily oral dose in children 6 to 11 years of age, and approximately 6 times the maximum recommended daily oral dose in children 6 months to 5 years of age on a mg/m^2 basis). No increased incidence of benign tumors was observed at a dietary dose of 4 mg/kg (approximately 2 times the maximum recommended daily oral dose in adults, equivalent to the maximum recommended daily oral dose in children 6 to 11 years of age and approximately 2 times the maximum recommended daily oral dose in children 6 months to 5 years of age on a mg/m^2 basis). The clinical significance of these findings during long-term use of XYZAL is not known.

Levocetirizine was not mutagenic in the Ames test, and not clastogenic in the human lymphocyte assay, the mouse lymphoma assay, and in vivo micronucleus test in mice.

In a fertility and general reproductive performance study in mice, cetirizine did not impair fertility at an oral dose of 64 mg/kg (approximately 25 times the recommended daily oral dose in adults on a mg/m^2 basis).

13.2 Animal Toxicology

Reproductive Toxicology Studies

In rats and rabbits, levocetirizine was not teratogenic at oral doses up to 200 and 120 mg/kg, respectively, (approximately 320 and 390, respectively, times the maximum recommended daily oral dose in adults on a mg/m^2 basis).

In mice, cetirizine caused retarded pup weight gain during lactation at an oral dose in dams of 96 mg/kg (approximately 40 times the maximum recommended daily oral dose in adults on a mg/m^2 basis).

14 CLINICAL STUDIES

Enter section text here

14.1 Seasonal and Perennial Allergic Rhinitis

Adults and Adolescents 12 Years of Age and Older

The efficacy of XYZAL was evaluated in six randomized, placebo-controlled, double-blind clinical trials in adult and adolescent patients 12 years and older with symptoms of seasonal allergic rhinitis or perennial allergic rhinitis. The six clinical trials include three dose-ranging trials of 2 to 4 weeks duration, one 2-week efficacy trial in patients with seasonal allergic rhinitis, and two efficacy trials (one 6-week and one 6-month) in patients with perennial allergic rhinitis.

These trials included a total of 2412 patients (1068 males and 1344 females) of whom 265 were adolescents 12 to 17 years of age. Efficacy was assessed using a total symptom score from patient recording of 4 symptoms (sneezing, rhinorrhea, nasal pruritus, and ocular pruritus) in five studies and 5 symptoms (sneezing, rhinorrhea, nasal pruritus, ocular pruritus, and nasal congestion) in one study. Patients recorded symptoms using a 0-3 categorical severity scale (0 = absent, 1 = mild, 2 = moderate, 3 = severe) once daily in the evening reflective of the 24 hour treatment period. In one study, patients also recorded these symptoms in an instantaneous (1 hour before the next dose) manner. The primary endpoint was the mean total symptom score averaged over the first week and over 2 weeks for seasonal allergic rhinitis trials, and 4 weeks for perennial allergic rhinitis trials.

The three dose-ranging trials were conducted to evaluate the efficacy of XYZAL 2.5, 5, and 10 mg once daily in the evening. One trial was 2 weeks in duration conducted in patients with seasonal allergic rhinitis, and two trials were 4 weeks in duration conducted in patients with perennial allergic rhinitis. In these trials, each of the three doses of XYZAL demonstrated greater decrease in the reflective total symptom score than placebo and the difference was statistically significant for all three doses in two of the studies. Results for two of these trials are shown in Table 4.

Table 4 Mean Reflective Total Symptom Score* in Allergic Rhinitis Dose-Ranging Trials
Treatment | N | Baseline | On Treatment Adjusted Mean | Difference Estimate | from Placebo 95% CI | p-value
Seasonal Allergic Rhinitis | Trial | – Reflective total symptom score
XYZAL 2.5 mg | 116 | 7.83 | 4.27 | 0.91 | (0.37, 1.45) | 0.001
XYZAL 5 mg | 115 | 7.45 | 4.06 | 1.11 | (0.57, 1.65) | less than 0.001
XYZAL 10 mg | 118 | 7.15 | 3.57 | 1.61 | (1.07, 21.5) | less than 0.001
Placebo | 118 | 7.94 | 5.17
Perennial Allergic Rhinitis | Trial | – Reflective total symptom score
XYZAL 2.5 mg | 133 | 7.14 | 4.12 | 1.17 | (0.71, 1.63) | less than 0.001
XYZAL 5 mg | 127 | 7.18 | 4.07 | 1.22 | (0.76, 1.69) | less than 0.001
XYZAL 10 mg | 129 | 7.58 | 4.19 | 1.10 | (0.64, 1.57) | less than 0.001
Placebo | 128 | 7.22 | 5.29

*
Total symptom score is the sum of individual symptoms of sneezing, rhinorrhea, nasal pruritus, and ocular pruritus as assessed by patients on a 0-3 categorical severity scale.

One clinical trial was designed to evaluate the efficacy of XYZAL 5 mg once daily in the evening compared with placebo in patients with seasonal allergic rhinitis over a 2-week treatment period. In this trial, XYZAL 5 mg demonstrated a greater decrease from baseline in the reflective and instantaneous total symptom score than placebo, and the difference was statistically significant (see Table 5). The results of the instantaneous total symptom score support efficacy at the end of the dosing interval.

One clinical trial evaluated the efficacy of XYZAL 5 mg once daily in the evening compared to placebo in patients with perennial allergic rhinitis over a 6-week treatment period. Another trial conducted over a 6-month treatment period assessed efficacy at 4 weeks. XYZAL 5 mg demonstrated a greater decrease from baseline in the reflective total symptom score than placebo and the difference from placebo was statistically significant. Results of one of these trials are shown in Table 5.

Table 5 Mean Reflective Total Symptom Score* and Instantaneous Total Symptom Score in Allergic Rhinitis Trials
Treatment | N | Baseline | On Treatment Adjusted Mean | Difference Estimate | from Placebo 95% CI | p-value
Seasonal Allergic Rhinitis | Trial | – Reflective total symptom score
XYZAL 5 mg | 118 | 8.40 | 5.20 | .089 | (0.30, 1.47) | 0.003
Placebo | 117 | 8.50 | 6.09
Seasonal Allergic Rhinitis | Trial | – Instantaneous total symptom score
XYZAL 5 mg | 118 | 7.24 | 4.58 | 0.73 | (0.17, 1.28) | 0.011
Placebo | 117 | 7.48 | 5.30
Perennial Allergic Rhinitis | Trial | – Reflective total symptom score
XYZAL 5 mg | 150 | 7.69 | 3.93 | 1.17 | (0.70, 1.64) | less than 0.001
Placebo | 142 | 7.44 | 5.10

*
Total symptom score is the sum of individual symptoms of sneezing, rhinorrhea, nasal pruritus, and ocular pruritus as assessed by patients on a 0-3 categorical severity scale.

Onset of action was evaluated in two environmental exposure unit studies in allergic rhinitis patients with a single dose of XYZAL 2.5 or 5 mg. XYZAL 5 mg was found to have an onset of action 1 hour after oral intake. Onset of action was also assessed from the daily recording of symptoms in the evening before dosing in the seasonal and perennial allergic rhinitis trials. In these trials, onset of effect was seen after 1 day of dosing.

Pediatric Patients Less than 12 Years of Age

There are no clinical efficacy trials with XYZAL 2.5 mg once daily in pediatric patients under 12 years of age, and no clinical efficacy trials with XYZAL 1.25 mg once daily in pediatric patients 6 months to 5 years of age. The clinical efficacy of XYZAL in pediatric patients under 12 years of age has been extrapolated from adult clinical efficacy trials based on pharmacokinetic comparisons [seeUse in Specific Populations (8.4)].

14.2 Chronic Idiopathic Urticaria

Adult Patients 18 Years of Age and Older

The efficacy of XYZAL for the treatment of the uncomplicated skin manifestations of chronic idiopathic urticaria was evaluated in two multi-center, randomized, placebo-controlled, double-blind clinical trials of 4 weeks duration in adult patients 18 to 85 years of age with chronic idiopathic urticaria. The two trials included one 4-week dose-ranging trial and one 4-week single-dose level efficacy trial. These trials included 423 patients (139 males and 284 females). Most patients (greater than 90%) were Caucasian and the mean age was 41. Of these patients, 146 received XYZAL 5 mg once daily in the evening. Efficacy was assessed based on patient recording of pruritus severity on a severity score of 0–3 (0 = none to 3 = severe). The primary efficacy endpoint was the mean reflective pruritus severity score over the first week and over the entire treatment period. Additional efficacy variables were the instantaneous pruritus severity score, the number and size of wheals, and duration of pruritus.

The dose-ranging trial was conducted to evaluate the efficacy of XYZAL 2.5, 5, and 10 mg once daily in the evening. In this trial, each of the three doses of XYZAL demonstrated greater decrease in the reflective pruritus severity score than placebo and the difference was statistically significant for all three doses (see Table 6).

The single dose level trial evaluated the efficacy of XYZAL 5 mg once daily in the evening compared to placebo in patients with chronic idiopathic urticaria over a 4-week treatment period. XYZAL 5 mg demonstrated a greater decrease from baseline in the reflective pruritus severity score than placebo and the difference from placebo was statistically significant.

Duration of pruritus, number and size of wheals, and instantaneous pruritus severity score also showed significant improvement over placebo. The significant improvement in the instantaneous pruritus severity score over placebo confirmed end of dosing interval efficacy (see Table 6).

Table 6 Mean Reflective Pruritus Severity Score in Chronic Idiopathic Urticaria Trials
Treatment | N | Baseline | On Treatment Adjusted Mean | Difference Estimate | from Placebo 95% CI | p-value
Dose-Ranging | Trial | - Reflective pruritus severity score
XYZAL 2.5 mg | 69 | 2.08 | 1.02 | 0.82 | (0.58, 1.06) | less than 0.001
XYZAL 5 mg | 62 | 2.07 | 0.92 | 0.91 | (0.66, 1.16) | less than 0.001
XYZAL 10 mg | 55 | 2.04 | 0.73 | 1.11 | (0.85, 1.37) | less than 0.001
Placebo | 60 | 2.25 | 1.84
Chronic Idiopathic Urticaria | Trial | - Reflective pruritus severity score
XYZAL 5 mg | 80 | 2.07 | 0.94 | 0.62 | (0.38, 0.86) | less than 0.001
Placebo | 82 | 2.06 | 1.56

Pediatric Patients

There are no clinical efficacy trials in pediatric patients with chronic idiopathic urticaria [see Use in Specific Populations (8.4)].

16 HOW SUPPLIED/STORAGE AND HANDLING

XYZAL tablets are white, film-coated, oval-shaped, scored, imprinted (with the letter Y in red color on both halves of the scored tablet) and contain 5 mg levocetirizine dihydrochloride. They are supplied in bottles of:

30 Tablets NDC 54868-5829-0

XYZAL oral solution is a clear, colorless liquid containing 0.5 mg of levocetirizine dihydrochloride per mL.

Oral solution in 5 oz glass bottles NDC 54868-6115-0

Storage:

Store at 20-25°C (68-77°F); excursions permitted to 15‑30°C (59-86°F) [see USP Controlled Room Temperature].

17 PATIENT COUNSELING INFORMATION

Enter section text here

17.1 Activities Requiring Mental Alertness

Patients should be cautioned against engaging in hazardous occupations requiring complete mental alertness, and motor coordination such as operating machinery or driving a motor vehicle after ingestion of XYZAL.

17.2 Concomitant Use of Alcohol and other Central Nervous System Depressants

Concurrent use of XYZAL with alcohol or other central nervous system depressants should be avoided because additional reduction in mental alertness may occur.

17.3 Dosing of XYZAL

The daily dose in adults and adolescents 12 years of age and older should not exceed 5 mg once daily in the evening. In children 6 to 11 years of age the recommended dose is 2.5 mg once daily in the evening. Patients should be advised to not ingest more than the recommended dose of XYZAL because of the increased risk of somnolence at higher doses.

Manufactured by

UCB Farchim SA

CH-1630 Bulle
(Switzerland)
For UCB Inc.
Smyrna,GA 30080 (USA)

XYZAL is a registered trademark of the UCB Group of companies.

©2008 UCB, Inc. All rights reserved.

Repackaging and/or Relabeling of "Additional Barcode" by:
Physicians Total Care, Inc.
Tulsa, OK 74146

PRINCIPAL DISPLAY PANEL

Xyzal®
(Levocetirizine Dihydrochloride)
5 mg tablet
Rx only

Xyzal®
(Levocetirizine Dihydrochloride)
5 mL oral solution
Rx only